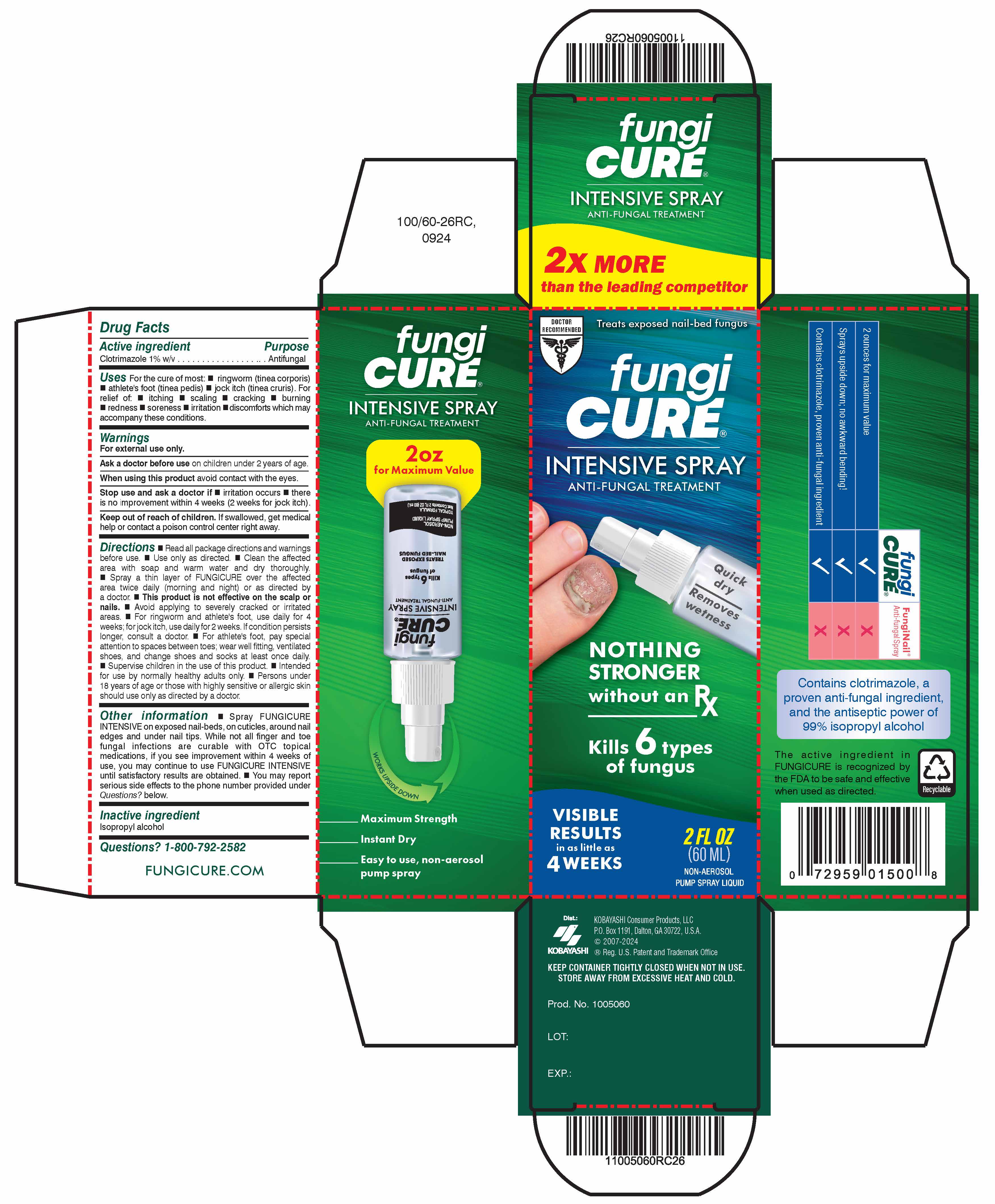 DRUG LABEL: Fungicure
NDC: 52389-600 | Form: LIQUID
Manufacturer: Kobayashi Healthcare International, Inc.
Category: otc | Type: HUMAN OTC DRUG LABEL
Date: 20260107

ACTIVE INGREDIENTS: CLOTRIMAZOLE 10 mg/1 mL
INACTIVE INGREDIENTS: ISOPROPYL ALCOHOL

Fungicure Intensive

Active ingredient

Clotrimazole 1% w/v

Purpose

Antifungal

Uses

For the cure of most:

- ringworm (tinea corporis)
- athlete's foot (tinea pedis)
- jock itch (tinea cruris)

For relief of:

- itching
- scaling
- cracking
- burning
- redness
- soreness
- irritation
- discomforts which may accompany these conditions

Warnings

For external use only.

Ask a doctor before use on children under 2 years of age.

When using this product avoid contact with the eyes.

Stop use and ask a doctor if

- irritation occurs
- there is no improvement within 4 weeks (2 weeks for jock itch)

Keep out of reach of children. If swallowed, get medical help or contact a poison control center right away.

Directions

- Read all package directions and warnings before use.
- Use only as directed.
- Clean the affected area with soap and warm water and dry thoroughly.
- Spray a thin layer of FUNGICURE over the affected area twice daily (morning and night) or as directed by a doctor.
- This product is not effective on the scalp or nails.
- Avoid applying to severely cracked or irritated areas.
- For ringworm and athlete's foot, use daily for 4 weeks; for jock itch, use daily for 2 weeks. If condition persists longer, consult a doctor.
- For athlete's foot, pay special attention to spaces between toes; wear well fitting, ventilated shoes, and change shoes and socks at least once daily.
- Supervise children in the use of this product.
- Intended for use by normally healthy adults only.
- Persons under 18 years of age or those with highly sensitive or allergic skin should use only as directed by a doctor.

Other information

Spray FUNGICURE INTENSIVE on exposed nail-beds, on cuticles, around nail edges and under nail tips. While not all finger and toe fungal infections are curable with OTC topical medications, if you see improvement within 4 weeks of use, you may continue to use FUNGICURE INTENSIVE until satisfactory results are obtained. You may report serious side effects to the phone number provided under Questions? below.

Inactive ingredient

Isopropyl alcohol

Questions? 1-800-792-2582

Package Insert

Maximum Strength

FUNGICURE INTENSIVE

Anti-Fungal Treatment

Cures Finger and Toe Area Fungal Infections

Kills 6 Types of Fungus on Exposed Nail-Beds

WHAT IS FUNGUS INFECTION OF THE FINGER AND TOES?

Common topical fungus infections of the fingers and toes are caused by a variety of fungi; actual living organisms (members of the yeast and mold family) which thrive in dark, moist conditions. Using small breaches in the skin's surface, these organisms can cause infection by contact with infected surfaces, animals or people. Once infection starts, spreading may occur. For example, infected fingers and toes may infect other fingers and toes. Although such infections often develop slowly, they may be difficult to eliminate if not treated promptly with an effective anti-fungal medicine like FUNGICURE.

HOW DO YOU KNOW IF YOU HAVE A TOPICAL FUNGUS INFECTION?

Some topical fungal infections may present themselves on the skin surface as ring-like formations with clear centers; this is commonly called ringworm. Athlete's foot fungus and jock itch fungus, when in the finger and toe areas, are often characterized by scaling of skin, burning, cracking, itching, and related discomforts. When nails become infected, they may appear to become opaque (cloudy white), thickened, brittle, easily broken, and in some cases, discolored (greenish/brown).

UNDERSTANDING AND TREATING A NAIL AREA INFECTION:

Fungal infections of the nail areas are often caused by the same fungi that lead to athlete's foot, jock itch, and ringworm infections elsewhere on the body. These fungi can infect the entire area around the nails including the cuticles, the nail beds, and even the nails themselves. When infected finger/toe nails are intact, over-the-counter topical anti-fungal treatments may not be able to penetrate the nail and kill the fungus; this is why all OTC topical treatments must indicate they are not effective on the nails. However, in instances of advanced infection, the nails often are not not intact; they may be missing, cracked open or lifted away, exposing the infected nail bed. In these instances FUNGICURE Intensive, with its powerful anti-fungal formula, can reach and kill nail bed fungus by direct application or related capillary action. FUNGICURE cures the infection, allowing the natural regrowth of healthy looking tissue.

NOTE: Fungal infections which are isolated beneath an intact nail or embedded within the nail itself may require consultation from a doctor for proper treatment.

HOW FUNGICURE INTENSIVE WORKS:

MAXIMUM STRENGTH FUNGICURE Intensive contains Clotrimazole, a widely recognized anti-fungal ingredient that has been proven to be effective aginst 6 types of fungus such as E. floccosum, T. mentagrophytes, M. canis, M. gypseum, T. tonsurans and T. rubrum.

When applied as directed, FUNGICURE Intensive acts promptly to target, destroy, and prevent the spread of infection by inhibiting the growth and reproduction of fungal cells.

PROMPT ACTION AND PROPER TREATMENT:

Early treatment of fungal infections is important. If you suspect that you may have a fungal infection, consult your doctor promptly for advice and proper diagnosis. You may wish to show him/her FUNGICURE Intensive and discuss its use. For best results, once treatment is started with FUNGICURE Intensive, it is important to carefully follow the treatment instructions on the package until satisfactory results are achieved or advised further by a doctor.

NOTE: Noticeable improvement may be expected within 4 weeks in the case of most ringworm (tinea corporis) and athlete's foot (tinea pedis), two weeks for most jock itch (tinea cruris). Consult your doctor for advice if noticeable improvement is not eveident by this time or if condition persists or worsens.

Active ingredient: Clotrimazole 1% w/v

Uses: For the cure of most:

- ringworm (tinea corporis)
- athlete's foot (tinea pedis)
- jock itch (tinea cruris)

For relief of

- itching
- scaling
- cracking
- burning
- redness
- soreness
- irritation
- discomforts which may accompany these conditions.

Warnings: For external use only.

Ask a doctor before use on children under 2 years of age.

When using this product avoid contact with the eyes.

Stop use and ask a doctor if irritation occurs or there is no improvement within 4 weeks (2 weeks for jock itch).

Keep out of reach of children. If swallowed, get medical help or contact a poison control center right away.

Directions: Read all package directions and warnings before use. Use only as directed. Clean the affected area with soap and warm water and dry thoroughly. Spray a thin layer of FUNGICURE over the affected area twice daily (morning and night), or as directed by a doctor. This product is not effective on the scalp or nails. Avoid applying to severely cracked or irritated areas. For ringworm and athlete's foot, use daily for 4 weeks; for jock itch, use daily for 2 weeks. If condition persists longer, consult a doctor. For athlete's foot, pay special attention to spaces between toes; wear well fitting, ventilated shoes, and change shoes and socks at least once daily. Supervise children in the use of this product. Intended for use by normally healthy adults only. Persons under 18 years of age or those with highly sensitive or allergic skin should use only as directed by a doctor.

Other Information: Spray FUNGICURE INTENSIVE on exposed nail-beds, on cuticles, around nail edges and under nail tips. While not all finger and toe fungal infections are curable with OTC topical medications, if you see improvement within 4 weeks of use, you may continue to use FUNGICURE INTENSIVE until satisfactory results are obtained. You may report serious side effects to the phone number provided under Questions? below.

Inactive ingredient: Isopropyl alcohol

Questions? 1-800-792-2582

How Supplied: 2 fl. oz. (60ml) non-aerosol pump spray.

Storage: Keep container closed (capped) when not in use. Store away from excessive heat or cold.

The active ingredient in FUNGICURE has been recognized to be safe and effective by an FDA Expert Advisory Panel, when used as directed.